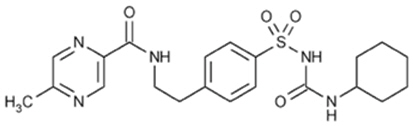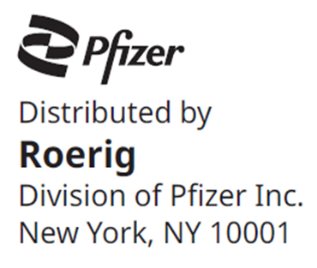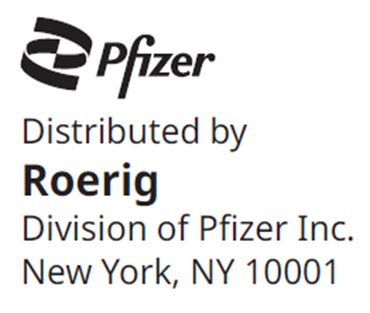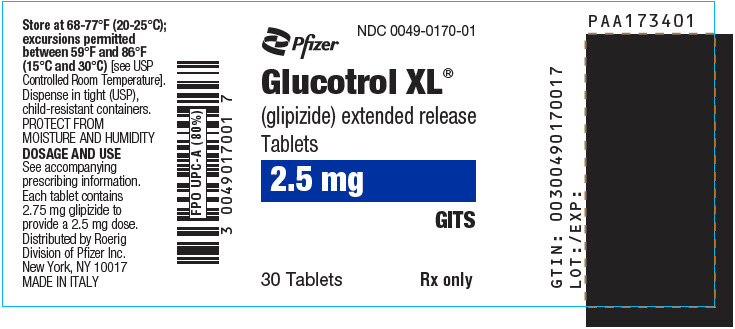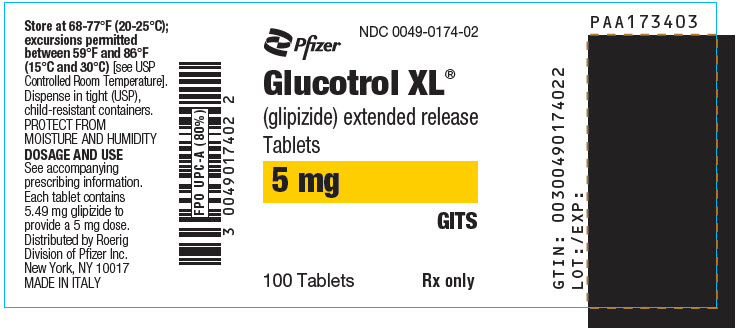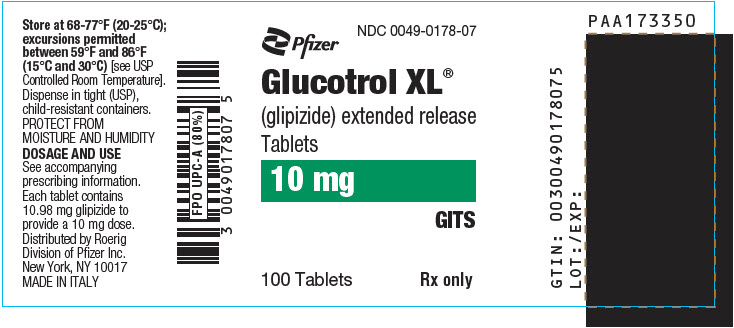 DRUG LABEL: Glucotrol
NDC: 0049-0170 | Form: TABLET, EXTENDED RELEASE
Manufacturer: Roerig
Category: prescription | Type: HUMAN PRESCRIPTION DRUG LABEL
Date: 20250402

ACTIVE INGREDIENTS: GLIPIZIDE 2.5 mg/1 1
INACTIVE INGREDIENTS: POLYETHYLENE GLYCOL, UNSPECIFIED; HYPROMELLOSE, UNSPECIFIED; MAGNESIUM STEARATE; SODIUM CHLORIDE; FERRIC OXIDE RED; CELLULOSE ACETATE

HIGHLIGHTS OF PRESCRIBING INFORMATION

These highlights do not include all the information needed to use GLUCOTROL XL safely and effectively. See full prescribing information for GLUCOTROL XL.
GLUCOTROL XL® (glipizide) extended release tablets, for oral use
Initial U.S. Approval: 1994

1 INDICATIONS AND USAGE

GLUCOTROL XL is a sulfonylurea indicated as an adjunct to diet and exercise to improve glycemic control in adults with type 2 diabetes mellitus

Limitations of Use: Not for treatment of type 1 diabetes or diabetic ketoacidosis

2 DOSAGE AND ADMINISTRATION

- Recommended starting dose is 5 mg once daily. Dose adjustment can be made based on the patient's glycemic control. Maximum recommended dose is 20 mg once daily (2.1).
- Administer with breakfast or the first meal of the day (2.1).
- For combination therapy with other blood-glucose-lowering agents, initiate the agent at the lowest recommended dose, and observe patients for hypoglycemia (2.2).

3 DOSAGE FORMS AND STRENGTHS

Tablets: 2.5 mg, 5 mg, 10 mg (3).

4 CONTRAINDICATIONS

- Known hypersensitivity to glipizide or any of the product's ingredients (4).
- Hypersensitivity to sulfonamide derivatives (4).

5 WARNINGS AND PRECAUTIONS

- Hypoglycemia: May be severe. Ensure proper patient selection, dosing, and instructions, particularly in at-risk populations (e.g., elderly, renally impaired) and when used with other anti-diabetic medications (5.1).
- Hemolytic Anemia: Can occur if glucose 6-phosphate dehydrogenase (G6PD) deficient. Consider a non-sulfonylurea alternative (5.2).
- Potential Increased Risk of Cardiovascular Mortality with Sulfonylureas: Inform patient of risks, benefits and treatment alternatives (5.3).
- Macrovascular Outcomes: No clinical studies have established conclusive evidence of macrovascular risk reduction with GLUCOTROL XL or any other anti-diabetic drug (5.4).

6 ADVERSE REACTIONS

Most common adverse reactions (incidence > 3%) are dizziness, diarrhea, nervousness, tremor, hypoglycemia and flatulence (6.1).

To report SUSPECTED ADVERSE REACTIONS, contact Pfizer, Inc. at 1-800-438-1985 or FDA at 1-800-FDA-1088 or www.fda.gov/medwatch.

7 DRUG INTERACTIONS

- Certain medications may affect glucose metabolism, requiring GLUCOTROL XL dose adjustment and close monitoring of blood glucose (7.1).
- Miconazole: Monitor patients closely. Severe hypoglycemia can occur when GLUCOTROL and oral miconazole are used concomitantly (7.2, 12.3).
- Fluconazole: Monitor patients closely. An increase in GLUCOTROL AUC was seen after fluconazole administration (7.3, 12.3).
- Colesevelam: GLUCOTROL XL should be administered at least 4 hours prior to colesevelam (7.4, 12.3).

8 USE IN SPECIFIC POPULATIONS

- Geriatric, Hepatically Impaired Patients: At risk for hypoglycemia with GLUCOTROL XL. Use caution in dose selection and titration, and monitor closely (8.5, 8.6).

FULL PRESCRIBING INFORMATION

1 INDICATIONS AND USAGE

GLUCOTROL XL is indicated as an adjunct to diet and exercise to improve glycemic control in adults with type 2 diabetes mellitus.

1.1 Limitations of Use

GLUCOTROL XL is not recommended for the treatment of type 1 diabetes mellitus or diabetic ketoacidosis.

2 DOSAGE AND ADMINISTRATION

2.1 Recommended Dosing

GLUCOTROL XL should be administered orally with breakfast or the first main meal of the day.

The recommended starting dose of GLUCOTROL XL is 5 mg once daily. Start patients at increased risk for hypoglycemia (e.g. the elderly or patients with hepatic insufficiency) at 2.5 mg [see Use in Specific Population (8.5, 8.6)].

Dosage adjustment can be made based on the patient's glycemic control. The maximum recommended dose is 20 mg once daily.

Patients receiving immediate release glipizide may be switched to GLUCOTROL XL once daily at the nearest equivalent total daily dose.

2.2 Use with Other Glucose Lowering Agents

When adding GLUCOTROL XL to other anti-diabetic drugs, initiate GLUCOTROL XL at 5 mg once daily. Start patients at increased risk for hypoglycemia at a lower dose.

When colesevelam is coadministered with glipizide ER, maximum plasma concentration and total exposure to glipizide is reduced. Therefore, GLUCOTROL XL should be administered at least 4 hours prior to colesevelam.

3 DOSAGE FORMS AND STRENGTHS

GLUCOTROL XL (glipizide) Extended Release tablets:

2.5 mg, blue and imprinted with "GLUCOTROL XL 2.5" or "GXL 2.5" on one side

5 mg, white and imprinted with "GLUCOTROL XL 5" or "GXL 5" on one side

10 mg, white and imprinted with "GLUCOTROL XL 10" or "GXL 10" on one side

4 CONTRAINDICATIONS

Glipizide is contraindicated in patients with:

- Known hypersensitivity to glipizide or any of the product's ingredients.
- Hypersensitivity to sulfonamide derivatives.

5 WARNINGS AND PRECAUTIONS

5.1 Hypoglycemia

All sulfonylurea drugs, including GLUCOTROL XL, are capable of producing severe hypoglycemia [see Adverse Reactions (6)]. Concomitant use of GLUCOTROL XL with other anti-diabetic medication can increase the risk of hypoglycemia. A lower dose of GLUCOTROL XL may be required to minimize the risk of hypoglycemia when combining it with other anti-diabetic medications.

Educate patients to recognize and manage hypoglycemia. When initiating and increasing GLUCOTROL XL in patients who may be predisposed to hypoglycemia (e.g., the elderly, patients with renal impairment, patients on other anti-diabetic medications) start at 2.5 mg. Debilitated or malnourished patients, and those with adrenal, pituitary, or hepatic impairment are particularly susceptible to the hypoglycemic action of anti-diabetic medications. Hypoglycemia is also more likely to occur when caloric intake is deficient, after severe or prolonged exercise, or when alcohol is ingested.

The patient's ability to concentrate and react may be impaired as a result of hypoglycemia. Early warning symptoms of hypoglycemia may be different or less pronounced in patients with autonomic neuropathy, the elderly, and in patients who are taking beta-adrenergic blocking medications or other sympatholytic agents. These situations may result in severe hypoglycemia before the patient is aware of the hypoglycemia.

These impairments may present a risk in situations where these abilities are especially important, such as driving or operating other machinery. Severe hypoglycemia can lead to unconsciousness or convulsions and may result in temporary or permanent impairment of brain function or death.

5.2 Hemolytic Anemia

Treatment of patients with glucose 6-phosphate dehydrogenase (G6PD) deficiency with sulfonylurea agents, including GLUCOTROL XL, can lead to hemolytic anemia. Avoid use of GLUCOTROL XL in patients with G6PD deficiency. In post marketing reports, hemolytic anemia has also been reported in patients who did not have known G6PD deficiency.

5.3 Increased Risk of Cardiovascular Mortality with Sulfonylureas

The administration of oral hypoglycemic drugs has been reported to be associated with increased cardiovascular mortality as compared to treatment with diet alone or diet plus insulin. This warning is based on the study conducted by the University Group Diabetes Program (UGDP), a long-term prospective clinical trial designed to evaluate the effectiveness of glucose-lowering drugs in preventing or delaying vascular complications in patients with type 2 diabetes mellitus. The study involved 823 patients who were randomly assigned to one of four treatment groups.

UGDP reported that patients treated for 5 to 8 years with diet plus a fixed dose of tolbutamide (1.5 grams per day) had a rate of cardiovascular mortality approximately 2½ times that of patients treated with diet alone. A significant increase in total mortality was not observed, but the use of tolbutamide was discontinued based on the increase in cardiovascular mortality, thus limiting the opportunity for the study to show an increase in overall mortality. Despite controversy regarding the interpretation of these results, the findings of the UGDP study provide an adequate basis for this warning. The patient should be informed of the potential risks and advantages of glipizide and of alternative modes of therapy.

Although only one drug in the sulfonylurea class (tolbutamide) was included in this study, it is prudent from a safety standpoint to consider that this warning may also apply to other oral hypoglycemic drugs in this class, in view of their close similarities in mode of action and chemical structure.

5.4 Macrovascular Outcomes

There have been no clinical studies establishing conclusive evidence of macrovascular risk reduction with GLUCOTROL XL or any other anti-diabetic drug.

5.5 Gastrointestinal Obstruction

There have been reports of obstructive symptoms in patients with known strictures in association with the ingestion of another drug with this non-dissolvable extended release formulation. Avoid use of GLUCOTROL XL in patients with preexisting severe gastrointestinal narrowing (pathologic or iatrogenic).

6 ADVERSE REACTIONS

The following serious adverse reactions are discussed in more detail below and elsewhere in the labeling:

- Hypoglycemia [see Warnings and Precautions (5.1)]
- Hemolytic anemia [see Warnings and Precautions (5.2)]

6.1 Clinical Trials Experience

Because clinical trials are conducted under widely varying conditions, adverse reaction rates observed in the clinical trials of a drug cannot be directly compared to rates in the clinical trials of another drug and may not reflect the rates observed in practice.

In clinical trials, 580 patients from 31 to 87 years of age received GLUCOTROL XL in doses from 5 mg to 60 mg in both controlled and open trials. The dosages above 20 mg are not recommended dosages. In these trials, approximately 180 patients were treated with GLUCOTROL XL for at least 6 months.

Table 1 summarizes the incidence of adverse reactions, other than hypoglycemia, that were reported in pooled double-blind, placebo-controlled trials in ≥3% of GLUCOTROL XL-treated patients and more commonly than in patients who received placebo.

Table 1: Incidence (%) of Adverse Reactions Reported in ≥3% of Patients Treated in Placebo-Controlled Clinical Trials and More Commonly in Patients Treated with GLUCOTROL XL (Excluding Hypoglycemia)
 | GLUCOTROL XL (%) (N=278) | Placebo (%) (N=69)
Adverse Effect
Dizziness | 6.8 | 5.8
Diarrhea | 5.4 | 0.0
Nervousness | 3.6 | 2.9
Tremor | 3.6 | 0.0
Flatulence | 3.2 | 1.4

Hypoglycemia

Of the 580 patients that received GLUCOTROL XL in clinical trials, 3.4% had hypoglycemia documented by a blood-glucose measurement <60 mg/dL and/or symptoms believed to be associated with hypoglycemia and 2.6% of patients discontinued for this reason. Hypoglycemia was not reported for any placebo patients.

Gastrointestinal Reactions

In clinical trials, the incidence of gastrointestinal (GI) side effects (nausea, vomiting, constipation, dyspepsia), occurred in less than 3% of GLUCOTROL XL-treated patients and were more common in GLUCOTROL XL-treated patients than those receiving placebo.

Dermatologic Reactions

In clinical trials, allergic skin reactions, i.e., urticaria occurred in less than 1.5% of treated patients and were more common in GLUCOTROL XL treated patients than those receiving placebo. These may be transient and may disappear despite continued use of glipizide XL; if skin reactions persist, the drug should be discontinued.

Laboratory Tests

Mild to moderate elevations of ALT, LDH, alkaline phosphatase, BUN and creatinine have been noted. The relationship of these abnormalities to glipizide is uncertain.

6.2 Postmarketing Experience

The following adverse reactions have been identified during post approval use of GLUCOTROL XL. Because these reactions are reported voluntarily from a population of uncertain size, it is not always possible to reliably estimate their frequency or establish a causal relationship to drug exposure.

- Abdominal pain
- Cholestatic and hepatocellular forms of liver injury accompanied by jaundice
- Leukopenia, agranulocytosis, thrombocytopenia, hemolytic anemia [see Warnings and Precautions (5.2)], aplastic anemia, pancytopenia
- Hepatic porphyria and disulfiram-like reactions
- Hyponatremia and the syndrome of inappropriate antidiuretic hormone (SIADH) secretion
- Rash
- There have been reports of gastrointestinal irritation and gastrointestinal bleeding with use of another drug with this non-dissolvable extended release formulation.

7 DRUG INTERACTIONS

7.1 Drugs Affecting Glucose Metabolism

A number of medications affect glucose metabolism and may require GLUCOTROL XL dose adjustment and close monitoring for hypoglycemia or worsening glycemic control.

The following are examples of medication that may increase the glucose lowering effect of GLUCOTROL XL, increase the susceptibility to and/or intensity of hypoglycemia: antidiabetic agents, ACE inhibitors, angiotensin II receptor blocking agents, disopyramide, fibrates, fluoxetine, monoamine oxidase inhibitors, pentoxifylline, pramlintide, propoxyphene, salicylates, somatostatin analogs (e.g., octreotide), sulfonamide antibiotics, nonsteroidal anti-inflammatory agents, chloramphenicol, probenecid, coumarins, voriconazole, H2 receptor antagonists, and quinolones. When these medications are administered to a patient receiving GLUCOTROL XL, monitor the patient closely for hypoglycemia. When these medications are discontinued from a patient receiving GLUCOTROL XL, monitor the patient closely for worsening glycemic control.

The following are examples of medication that may reduce the glucose-lowering effect of GLUCOTROL XL, leading to worsening glycemic control: atypical antipsychotics (e.g., olanzapine and clozapine), corticosteroids, danazol, diuretics, estrogens, glucagon, isoniazid, niacin, oral contraceptives, phenothiazines, progestogens (e.g., in oral contraceptives), protease inhibitors, somatropin, sympathomimetic agents (e.g., albuterol, epinephrine, terbutaline), thyroid hormones, phenytoin, nicotinic acid, and calcium channel blocking drugs. When such drugs are administered to patients receiving GLUCOTROL XL, monitor the patients closely for worsening glycemic control. When these medications are discontinued from patients receiving GLUCOTROL XL, monitor the patient closely for hypoglycemia.

Alcohol, beta-blockers, clonidine, and reserpine may lead to either potentiation or weakening of the glucose-lowering effect. Increased frequency of monitoring may be required when GLUCOTROL XL is co-administered with these drugs.

The signs of hypoglycemia may be reduced or absent in patients taking sympatholytic drugs such as beta-blockers, clonidine, guanethidine, and reserpine. Increased frequency of monitoring may be required when GLUCOTROL XL is co-administered with these drugs.

7.2 Miconazole

Monitor patients closely for hypoglycemia when Glucotrol XL is co-administered with miconazole. A potential interaction between oral miconazole and oral hypoglycemic agents leading to severe hypoglycemia has been reported [see Clinical Phamacology (12.3)].

7.3 Fluconazole

Monitor patients closely for hypoglycemia when Glucotrol XL is co-administered with fluconazole. Concomitant treatment with fluconazole increases plasma concentrations of glipizide, which may lead to hypoglycemia [see Clinical Pharmacology (12.3)].

7.4 Colesevelam

GLUCOTROL XL should be administered at least 4 hours prior to the administration of colesevelam. Colesevelam can reduce the maximum plasma concentration and total exposure of glipizide when the two are coadministered [see Clinical Pharmacology (12.3)].

8 USE IN SPECIFIC POPULATIONS

8.1 Pregnancy

Risk Summary

Available data from a small number of published studies and postmarketing experience with GLUCOTROL XL use in pregnancy over decades have not identified any drug associated risks for major birth defects, miscarriage, or adverse maternal outcomes. However, sulfonylureas (including glipizide) cross the placenta and have been associated with neonatal adverse reactions such as hypoglycemia. Therefore, GLUCOTROL XL should be discontinued at least two weeks before expected delivery (see Clinical Considerations). Poorly controlled diabetes in pregnancy is also associated with risks to the mother and fetus (see Clinical Considerations). In animal studies, there were no effects on embryofetal development following administration of glipizide to pregnant rats and rabbits during organogenesis at doses 833 times and 8 times the human dose based on body surface area, respectively. However, increased pup mortality was observed in rats administered glipizide from gestation day 15 throughout lactation at doses 2 times the maximum human dose based on body surface area (see Data).

The estimated background risk of major birth defects is 6–10% in women with pre-gestational diabetes with a HbA1c >7 and has been reported to be as high as 20–25% in women with HbA1c >10. The estimated background risk of miscarriage for the indicated population is unknown. In the U.S. general population, the estimated background risk of major birth defects and miscarriage in clinically recognized pregnancies is 2–4% and 15–20%, respectively.

Clinical Considerations

Disease-Associated Maternal and/or Embryo/Fetal Risk

Poorly-controlled diabetes in pregnancy increases the maternal risk for diabetic ketoacidosis, pre-eclampsia, miscarriage, preterm delivery, stillbirth, and delivery complications. Poorly controlled diabetes increases the fetal risk for major birth defects, stillbirth, and macrosomia related morbidity.

Fetal/Neonatal Adverse Reactions

Neonates of women with gestational diabetes who are treated with sulfonylureas during pregnancy may be at increased risk for neonatal intensive care admission and may develop respiratory distress, hypoglycemia, birth injury, and be large for gestational age. Prolonged severe hypoglycemia, lasting 4–10 days, has been reported in neonates born to mothers receiving a sulfonylurea at the time of delivery and has been reported with the use of agents with a prolonged half-life. Observe newborns for symptoms of hypoglycemia and respiratory distress and manage accordingly.

Dose adjustments during pregnancy and the postpartum period

Due to reports of prolonged severe hypoglycemia in neonates born to mothers receiving a sulfonylurea at the time of delivery, GLUCOTROL XL should be discontinued at least two weeks before expected delivery (see Fetal/Neonatal Adverse Reactions).

Data

Animal Data

In teratology studies in rats and rabbits, pregnant animals received daily oral doses of glipizide during the period of organogenesis at doses up to 2000 mg/kg/day and 10 mg/kg/day (approximately 833 and 8 times the human dose based on body surface area), respectively. There were no adverse effects on embryo-fetal development at any of the doses tested. In a peri- and postnatal study in pregnant rats, there was a reduced number of pups born alive following administration of glipizide from gestation day 15 throughout lactation through weaning at doses ≥5 mg/kg/day (about 2 times the recommended maximum human dose based on body surface area).

8.2 Lactation

Risk Summary

Breastfed infants of lactating women using GLUCOTROL XL should be monitored for symptoms of hypoglycemia (see Clinical Considerations). Although glipizide was undetectable in human milk in one small clinical lactation study; this result is not conclusive because of the limitations of the assay used in the study. There are no data on the effects of glipizide on milk production. The developmental and health benefits of breastfeeding should be considered along with the mother's clinical need for GLUCOTROL XL and any potential adverse effects on the breastfed child from GLUCOTROL XL or from the underlying maternal condition.

Clinical Considerations

Monitoring for adverse reactions

Monitor breastfed infants for signs of hypoglycemia (e.g., jitters, cyanosis, apnea, hypothermia, excessive sleepiness, poor feeding, seizures).

8.4 Pediatric Use

Safety and effectiveness in children have not been established.

8.5 Geriatric Use

There were no overall differences in effectiveness or safety between younger and older patients, but greater sensitivity of some individuals cannot be ruled out. Elderly patients are particularly susceptible to the hypoglycemic action of anti-diabetic agents. Hypoglycemia may be difficult to recognize in these patients. Therefore, dosing should be conservative to avoid hypoglycemia [see Dosage and Administration (2.1), Warnings and Precautions (5.1) and Clinical Pharmacology (12.3)].

8.6 Hepatic Impairment

There is no information regarding the effects of hepatic impairment on the disposition of glipizide. However, since glipizide is highly protein bound and hepatic biotransformation is the predominant route of elimination, the pharmacokinetics and/or pharmacodynamics of glipizide may be altered in patients with hepatic impairment. If hypoglycemia occurs in such patients, it may be prolonged and appropriate management should be instituted [see Dosage and Administration (2.1), Warnings and Precautions (5.1) and Clinical Pharmacology (12.3)].

10 OVERDOSAGE

Overdosage of sulfonylureas including GLUCOTROL XL can produce severe hypoglycemia. Mild hypoglycemic symptoms without loss of consciousness or neurologic findings should be treated with oral glucose. Severe hypoglycemic reactions with coma, seizure, or other neurological impairment are medical emergencies requiring immediate treatment. The patient should be treated with glucagon or intravenous glucose. Patients should be closely monitored for a minimum of 24 to 48 hours since hypoglycemia may recur after apparent clinical recovery. Clearance of glipizide from plasma may be prolonged in persons with liver disease. Because of the extensive protein binding of glipizide, dialysis is unlikely to be of benefit.

11 DESCRIPTION

GLUCOTROL XL (glipizide) is an oral sulfonylurea.

The Chemical Abstracts name of glipizide is 1-cyclohexyl-3-[[p-[2-(5-methylpyrazinecarboxamido)ethyl] phenyl]sulfonyl]urea. The molecular formula is C21H27N5O4S; the molecular weight is 445.55; the structural formula is shown below:

Glipizide is a whitish, odorless powder with a pKa of 5.9. It is insoluble in water and alcohols, but soluble in 0.1 N NaOH; it is freely soluble in dimethylformamide.

Each tablet contains 2.75 mg glipizide to provide a 2.5 mg dose.

Each tablet contains 5.49 mg glipizide to provide a 5 mg dose.

Each tablet contains 10.98 mg glipizide to provide a 10 mg dose.

Inert ingredients in the 2.5 mg, 5 mg and 10 mg formulations are: polyethylene oxide, hypromellose, magnesium stearate, sodium chloride, red ferric oxide, cellulose acetate, polyethylene glycol, Opadry® blue (OY-LS-20921)(2.5 mg tablets), Opadry® white (YS-2-7063)(5 mg and 10 mg tablet) and Opacode® Black Ink (S-1-17823).

System Components and Performance

GLUCOTROL XL Extended Release Tablet is similar in appearance to a conventional tablet. It consists, however, of an osmotically active drug core surrounded by a semipermeable membrane. The core itself is divided into two layers: an "active" layer containing the drug, and a "push" layer containing pharmacologically inert (but osmotically active) components. The membrane surrounding the tablet is permeable to water but not to drug or osmotic excipients. As water from the gastrointestinal tract enters the tablet, pressure increases in the osmotic layer and "pushes" against the drug layer, resulting in the release of drug through a small, laser-drilled orifice in the membrane on the drug side of the tablet.

The function of the GLUCOTROL XL Extended Release Tablet depends upon the existence of an osmotic gradient between the contents of the bi-layer core and fluid in the GI tract. The biologically inert components of the tablet remain intact during GI transit and are eliminated in the feces as an insoluble shell.

12 CLINICAL PHARMACOLOGY

12.1 Mechanism of Action

Glipizide primarily lowers blood glucose by stimulating the release of insulin from the pancreas, an effect dependent upon functioning beta cells in the pancreatic islets. Sulfonylureas bind to the sulfonylurea receptor in the pancreatic beta-cell plasma membrane, leading to closure of the ATP-sensitive potassium channel, thereby stimulating the release of insulin.

12.2 Pharmacodynamics

The insulinotropic response to a meal is enhanced with GLUCOTROL XL administration in diabetic patients. The postprandial insulin and C-peptide responses continue to be enhanced after at least 6 months of treatment. In two randomized, double-blind, dose-response studies comprising a total of 347 patients, there was no significant increase in fasting insulin in all GLUCOTROL XL-treated patients combined compared to placebo, although minor elevations were observed at some doses.

In studies of GLUCOTROL XL in subjects with type 2 diabete mellitus, once daily administration produced reductions in hemoglobin A1c, fasting plasma glucose and postprandial glucose. The relationship between dose and reduction in hemoglobin A1c was not established, however subjects treated with 20 mg had a greater reduction in fasting plasma glucose compared to subjects treated with 5 mg.

12.3 Pharmacokinetics

Absorption

The absolute bioavailability of glipizide was 100% after single oral doses in patients with type 2 diabetes mellitus. Beginning 2 to 3 hours after administration of GLUCOTROL XL, plasma drug concentrations gradually rise reaching maximum concentrations within 6 to 12 hours after dosing. With subsequent once daily dosing of GLUCOTROL XL, plasma glipizide concentrations are maintained throughout the 24 hour dosing interval with less peak to trough fluctuation than that observed with twice daily dosing of immediate release glipizide.

The mean relative bioavailability of glipizide in 21 males with type 2 diabetes mellitus after administration of 20 mg GLUCOTROL XL, compared to immediate release Glucotrol (10 mg given twice daily), was 90% at steady-state. Steady-state plasma concentrations were achieved by at least the fifth day of dosing with GLUCOTROL XL in 21 males with type 2 diabetes mellitus and patients younger than 65 years. No accumulation of drug was observed in patients with type 2 diabetes mellitus during chronic dosing with GLUCOTROL XL.

Administration of GLUCOTROL XL with food has no effect on the 2 to 3 hour lag time in drug absorption. In a single dose, food effect study in 21 healthy male subjects, the administration of GLUCOTROL XL immediately before a high fat breakfast resulted in a 40% increase in the glipizide mean Cmax value, which was significant, but the effect on the AUC was not significant. There was no change in glucose response between the fed and fasting state. Markedly reduced GI retention times of the GLUCOTROL XL tablets over prolonged periods (e.g., short bowel syndrome) may influence the pharmacokinetic profile of the drug and potentially result in lower plasma concentrations.

In a multiple dose study in 26 males with type 2 diabetes mellitus, the pharmacokinetics of glipizide were linear with GLUCOTROL XL in that the plasma drug concentrations increased proportionately with dose. In a single dose study in 24 healthy subjects, four 5-mg, two 10-mg, and one 20-mg GLUCOTROL XL tablets were bioequivalent. In a separate single dose study in 36 healthy subjects, four 2.5-mg GLUCOTROL XL tablets were bioequivalent to one 10-mg GLUCOTROL XL tablet.

Distribution

The mean volume of distribution was approximately 10 liters after single intravenous doses in patients with type 2 diabetes mellitus. Glipizide is 98–99% bound to serum proteins, primarily to albumin.

Metabolism

The major metabolites of glipizide are products of aromatic hydroxylation and have no hypoglycemic activity. A minor metabolite, an acetylamino-ethyl benzene derivative, which accounts for less than 2% of a dose, is reported to have 1/10 to 1/3 as much hypoglycemic activity as the parent compound.

Elimination

Glipizide is eliminated primarily by hepatic biotransformation: less than 10% of a dose is excreted as unchanged drug in urine and feces; approximately 90% of a dose is excreted as biotransformation products in urine (80%) and feces (10%).

The mean total body clearance of glipizide was approximately 3 liters per hour after single intravenous doses in patients with type 2 diabetes mellitus. The mean terminal elimination half-life of glipizide ranged from 2 to 5 hours after single or multiple doses in patients with type 2 diabetes mellitus.

Specific Populations

Pediatric:

Studies characterizing the pharmacokinetics of glipizide in pediatric patients have not been performed.

Geriatric:

There were no differences in the pharmacokinetics of glipizide after single dose administration to older diabetic subjects compared to younger healthy subjects [see Use in Specific Populations (8.5)].

Renal Impairment:

The pharmacokinetics of glipizide has not been evaluated in patients with varying degree of renal impairment. Limited data indicates that glipizide biotransformation products may remain in circulation for a longer time in subjects with renal impairment than that seen in subjects with normal renal function.

Hepatic Impairment:

The pharmacokinetics of glipizide has not been evaluated in patients with hepatic impairment.

Drug-drug Interactions

Miconazole

A potential interaction between oral miconazole and oral glipizide leading to severe hypoglycemia has been reported. Whether this interaction also occurs with the intravenous, topical, or vaginal preparations of miconazole is not known [see Drug Interactions (7.2)].

Fluconazole

Concomitant treatment with fluconazole increases plasma concentrations of glipizide. The effect of concomitant administration of Diflucan® (fluconazole) and Glucotrol has been demonstrated in a placebo controlled crossover study in healthy volunteers. All subjects received Glucotrol alone and following treatment with 100 mg of Diflucan® as a single daily oral dose for 7 days. The mean percentage increase in the glipizide AUC after fluconazole administration was 56.9% (range: 35 to 81%) [see Drug Interactions (7.3)].

Colesevelam

Colesevelam can reduce the maximum plasma concentration and total exposure of glipizide when the two are coadministered. In studies assessing the effect of colesevelam on the pharmacokinetics of glipizide ER in healthy volunteers, reductions in glipizide AUC0–∞ and Cmax of 12% and 13%, respectively were observed when colesevelam was coadministered with glipizide ER. When glipizide ER was administered 4 hours prior to colesevelam, there was no significant change in glipizide AUC0–∞ or Cmax, -4% and 0%, respectively [see Drug Interactions (7.4)].

13 NONCLINICAL TOXICOLOGY

13.1 Carcinogenesis, Mutagenesis, Impairment of Fertility

A twenty month study in rats and an eighteen month study in mice at doses up to 75 times the maximum human dose revealed no evidence of drug-related carcinogenicity. Bacterial and in vivo mutagenicity tests were uniformly negative. Studies in rats of both sexes at doses up to 20 times the human dose based on body surface area, showed no effects on fertility.

15 REFERENCES

1. Diabetes, 19, SUPP. 2: 747–830, 1970

16 HOW SUPPLIED/STORAGE AND HANDLING

GLUCOTROL XL (glipizide) Extended Release Tablets are supplied to provide 2.5 mg, 5 mg, and 10 mg round, biconvex tablets and imprinted with black ink as follows:

Table 2. GLUCOTROL XL Tablet Presentations
Tablet Strength | Tablet Color/Shape | Tablet Markings | Package Size | NDC Code
2.5 mg | Blue Round Biconvex | imprinted with "GXL 2.5" on one side | Bottles of 30 | NDC 0049-0170-01
5 mg | White Round Biconvex | imprinted with "GXL 5" on one side | Bottles of 100 Bottles of 500 | NDC 0049-0174-02 NDC 0049-0174-03
10 mg | White Round Biconvex | imprinted with "GXL 10" on one side | Bottles of 100 Bottles of 500 | NDC 0049-0178-07 NDC 0049-0178-08

STORAGE AND HANDLING

Recommended Storage: The tablets should be protected from moisture and humidity. Store at 68–77°F (20–25°C); excursions permitted between 59°F and 86°F (15°C and 30°C) [see USP Controlled Room Temperature].

17 PATIENT COUNSELING INFORMATION

Advise the patient to read the FDA-approved patient labeling (Patient Information).

Inform patients of the potential adverse reactions of GLUCOTROL XL including hypoglycemia. Explain the risks of hypoglycemia, its symptoms and treatment, and conditions that predispose to its development to patients and responsible family members. Also inform patients about the importance of adhering to dietary instructions, of a regular exercise program, and of regular testing of glycemic control.

Inform patients that GLUCOTROL XL should be swallowed whole. Inform patients that they should not chew, divide or crush tablets and they may occasionally notice in their stool something that looks like a tablet. In the GLUCOTROL XL tablet, the medication is contained within a non-dissolvable shell that has been specially designed to slowly release the drug so the body can absorb it.

Pregnancy

Advise females of reproductive potential to inform their prescriber of a known or suspected pregnancy [see Use in Specific Populations (8.1)].

Lactation

Advise breastfeeding women taking GLUCOTROL XL to monitor breastfed infants for signs of hypoglycemia (e.g., jitters, cyanosis, hypothermia, excessive sleepiness, poor feeding, seizures) [see Use in Specific Populations (8.2)].

This product's label may have been updated. For full prescribing information, please visit www.pfizer.com.

LAB-0113-17.0

PATIENT INFORMATION
GLUCOTROL XL (GL'UːKˌOTROL)
(glipizide)
extended release tablets

What is GLUCOTROL XL?

- GLUCOTROL XL is a prescription medicine you take by mouth used along with diet and exercise to lower blood sugar in adults with type 2 diabetes mellitus.
- GLUCOTROL XL is not for people with type 1 diabetes or people with diabetic ketoacidosis.

It is not known if GLUCOTROL XL is safe and effective in children under 18 years of age.

Who Should Not Take GLUCOTROL XL?
Do not use GLUCOTROL XL if you:

- have a condition called diabetic ketoacidosis
- have ever had an allergic reaction to glipizide or any of the other ingredients in GLUCOTROL XL. See the end of this Patient Information for a complete list of ingredients in GLUCOTROL XL.

What should I tell my doctor before taking GLUCOTROL XL?
Before you take GLUCOTROL XL, tell your healthcare provider if you:

- Have ever had a condition called diabetic ketoacidosis
- Have kidney or liver problems
- Have had a blockage or narrowing of your intestines due to illness or past surgery
- Have chronic (continuing) diarrhea
- Have glucose-6-phosphate dehydrogenase (G6PD) deficiency. This condition usually runs in families. People with G6PD deficiency who take GLUCOTROL XL may develop hemolytic anemia (fast breakdown of red blood cells).
- Are pregnant or might be pregnant. It is not known if GLUCOTROL XL will harm your unborn baby. If you are pregnant, talk to your healthcare provider about the best way to control your blood sugar while you are pregnant. You should not take GLUCOTROL XL during the last two weeks of pregnancy.
- Are breastfeeding or plan to breastfeed. It is not known if GLUCOTROL XL passes into your breast milk. You and your healthcare provider should decide the best way to feed your baby during treatment with GLUCOTROL XL.

Tell your doctor about all the medicines you take, including prescription and over-the-counter medicines, vitamins, and herbal supplements.
GLUCOTROL XL may affect the way other medicines work, and other medicines may affect how GLUCOTROL XL works.
Some medicines can affect how well GLUCOTROL XL works or may affect you blood sugar level.
Know the medicines you take. Keep a list of them and show it to your healthcare provider and pharmacist when you get a new medicine.

How should I take GLUCOTROL XL?

- Take GLUCOTROL XL exactly as your healthcare provider tells you to take it.
- Your healthcare provider will tell you how much GLUCOTROL XL to take and when to take it.
- Take GLUCOTROL XL by mouth, 1 time each day with breakfast or your first meal of the day.
- Each GLUCOTROL XL tablet will release the medicine slowly over 24 hours. This is why you take it only 1 time each day.
- Swallow the GLUCOTROL XL whole. Do not break, crush, dissolve, chew, or cut the tablet in half. This will damage the tablet and release too much medicine into your body at one time.
- When you take GLUCOTROL XL you may see something in your stool that looks like a tablet. This is the empty shell from the tablet. It is normal for the empty shell to pass with your bowel movement after medicine has been absorbed by your body.
- It is important to take GLUCOTROL XL every day to help keep your blood sugar level under good control. Your healthcare provider may change your dose depending on your blood sugar test results. If your blood sugar level is not under control, call your healthcare provider. Do not change your dose unless your healthcare provider tells you to.
- If you take too much GLUCOTROL XL, call your healthcare provider or go to the nearest emergency room right away.
  Your healthcare provider may tell you to take GLUCOTROL XL with other diabetes medicines. Low blood sugar can happen more often when GLUCOTROL XL is taken with other diabetes medicines. See "What are the possible side effects of GLUCOTROL XL?"
- Check your blood sugar as your healthcare provider tells you to.
- Stay on your prescribed diet and exercise program while taking GLUCOTROL XL.

What should I avoid while taking GLUCOTROL XL?

- Do not drink alcohol while taking GLUCOTROL XL. It can increase your chances of getting serious side effects.
- Do not drive, operate machinery, or do other dangerous activities until you know how GLUCOTROL XL affects you.

What are the possible side effects of GLUCOTROL XL?
GLUCOTROL XL can cause serious side effects, including:

- Low blood sugar. GLUCOTROL XL may cause low blood sugar. Signs and symptoms of low blood sugar may include:

- a cold clammy feeling
- unusual sweating
- dizziness
- weakness
- trembling
- shakiness

- hunger
- fast heartbeat
- headache
- blurred vision
- slurred speech
- tingling in the lips or hands

If you have signs or symptoms of low blood sugar, eat or drink something with sugar in it right away. If you do not feel better or your blood sugar level does not go up, call your healthcare provider or go to the nearest emergency room.
The most common side effects of GLUCOTROL XL include: dizziness, diarrhea, nervousness, tremor, and gas.
These are not all the possible side effects of GLUCOTROL XL. For more information, ask your healthcare provider or pharmacist.
Call your doctor for medical advice about side effects. You may report side effects to FDA at 1-800-FDA-1088.

How to store GLUCOTROL XL?

- Store GLUCOTROL XL at room temperature between 68°F to 77°F (20°C to 25°C).
- Store GLUCOTROL XL in a dry place, in its original container.

Keep GLUCOTROL XL and all medicines out of reach of children.

General information about the safe and effective use of GLUCOTROL XL.
Medicines are sometimes prescribed for purposes other than those listed in a patient information leaflet. Do not use GLUCOTROL XL for a condition for which it was not prescribed. Do not give GLUCOTROL XL to other people, even if they have the same symptoms you have. It may harm them.
This Patient Information summarizes the most important information about GLUCOTROL XL. If you would like more information, talk with your healthcare provider. You can ask your pharmacist or healthcare provider for information about GLUCOTROL XL that is written for healthcare professionals.
For more information about GLUCOTROL XL, you can visit the Pfizer internet site at www.pfizer.com.

What are the ingredients in GLUCOTROL XL?
Active ingredient: glipizide
Inactive ingredients: polyethylene oxide, hypromellose, magnesium stearate, sodium chloride, red ferric oxide, cellulose acetate, polyethylene glycol, Opadry® blue (OY-LS-20921), (2.5 mg tablets) Opadry® white (YS 2 7063), (5 mg and 10 mg tablet) Opacode® Black Ink (S-1-17823).

LAB-0115-8.0

This Patient Information has been approved by the U.S. Food and Drug Administration

Revised 08/2023

PRINCIPAL DISPLAY PANEL - 2.5 mg Tablet Bottle Label - NDC 0049-0170

Pfizer
NDC 0049-0170-01

Glucotrol XL ®
(glipizide) extended release
Tablets

2.5 mg

GITS

30 Tablets
Rx only

PRINCIPAL DISPLAY PANEL - 5 mg Tablet Bottle Label - NDC 0049-0174

Pfizer
NDC 0049-0174-02

Glucotrol XL ®
(glipizide) extended release
Tablets

5 mg

GITS

100 Tablets
Rx only

PRINCIPAL DISPLAY PANEL - 10 mg Tablet Bottle Label - NDC 0049-0178

Pfizer
NDC 0049-0178-07

Glucotrol XL ®
(glipizide) extended release
Tablets

10 mg

GITS

100 Tablets
Rx only